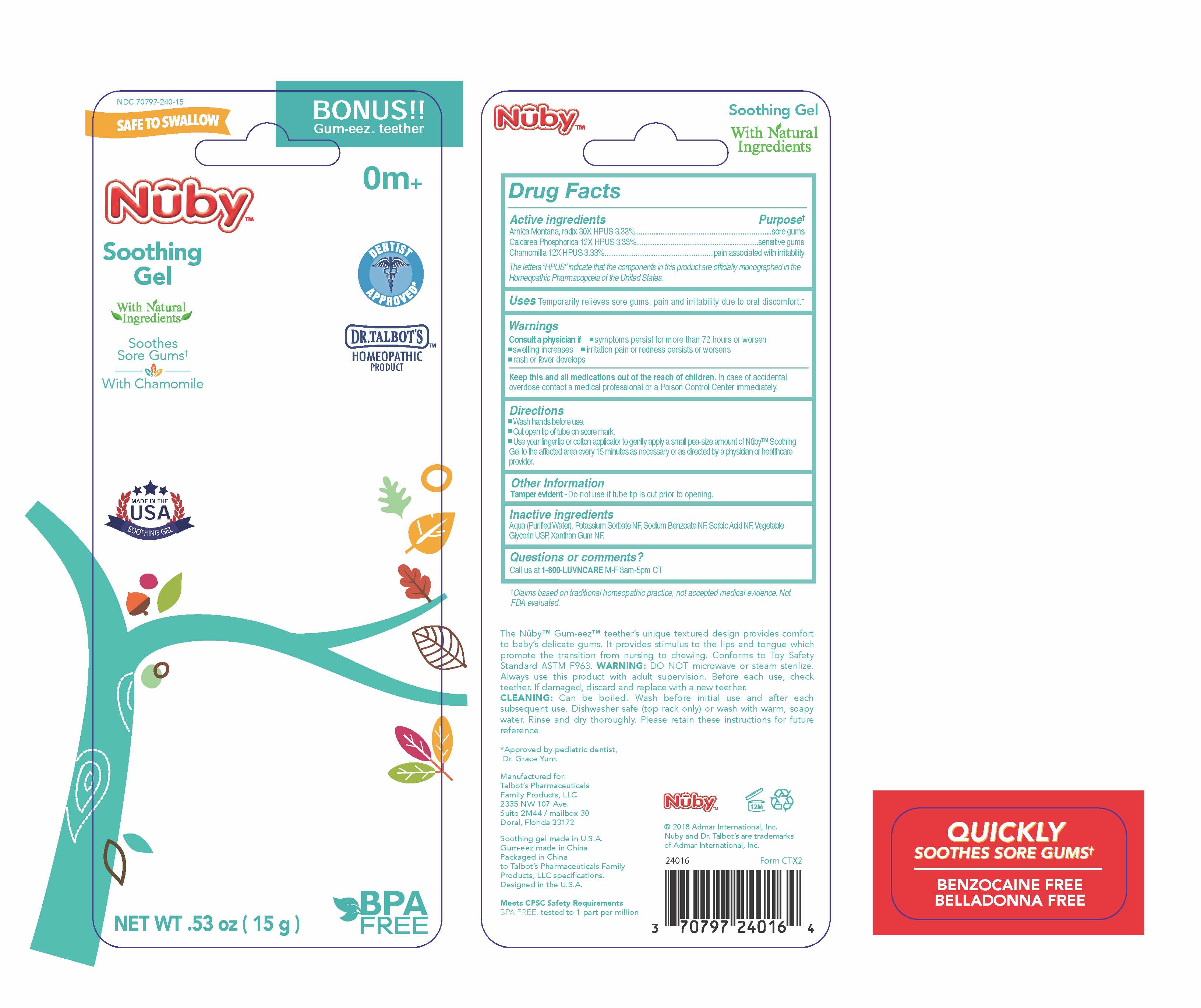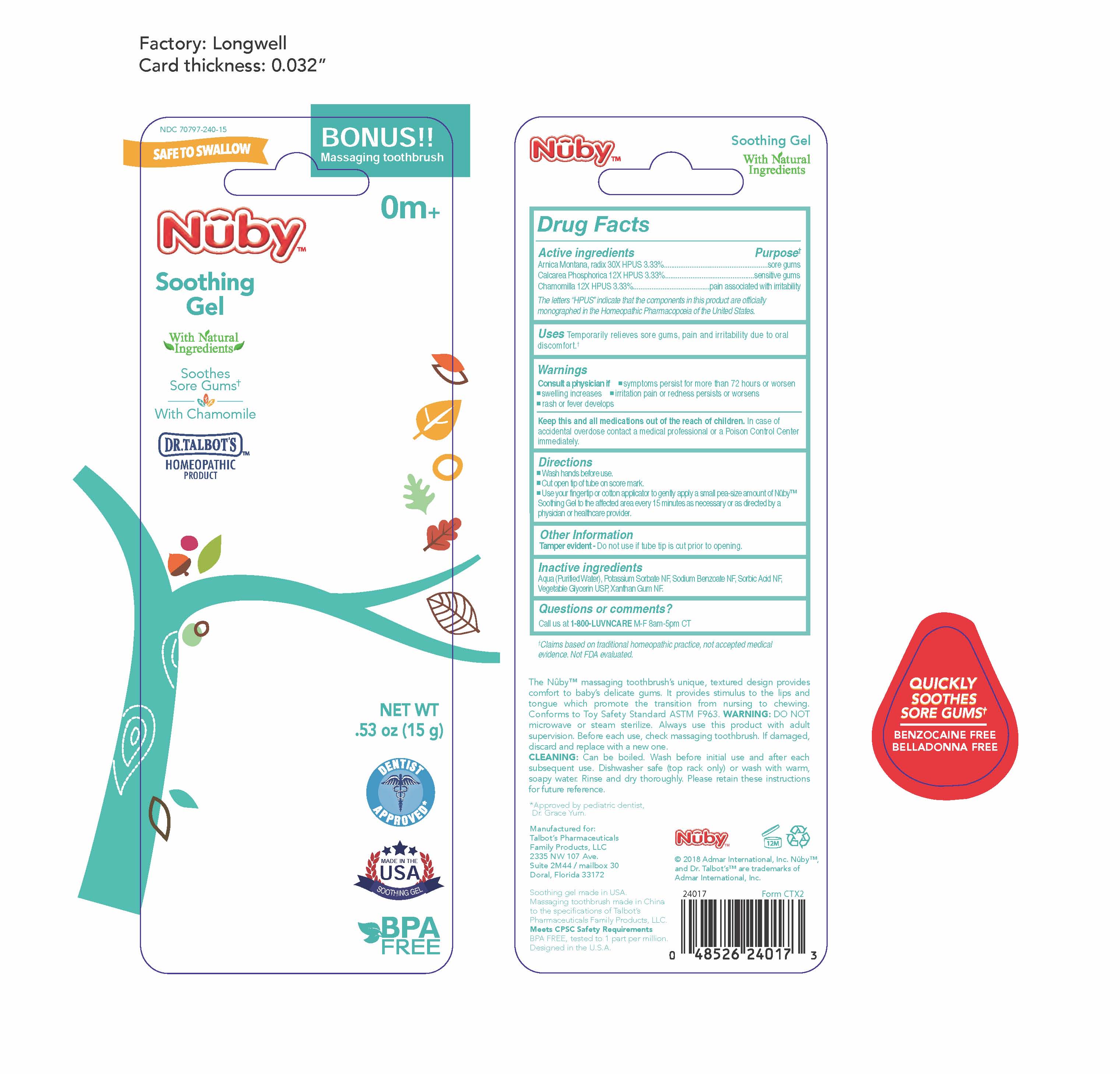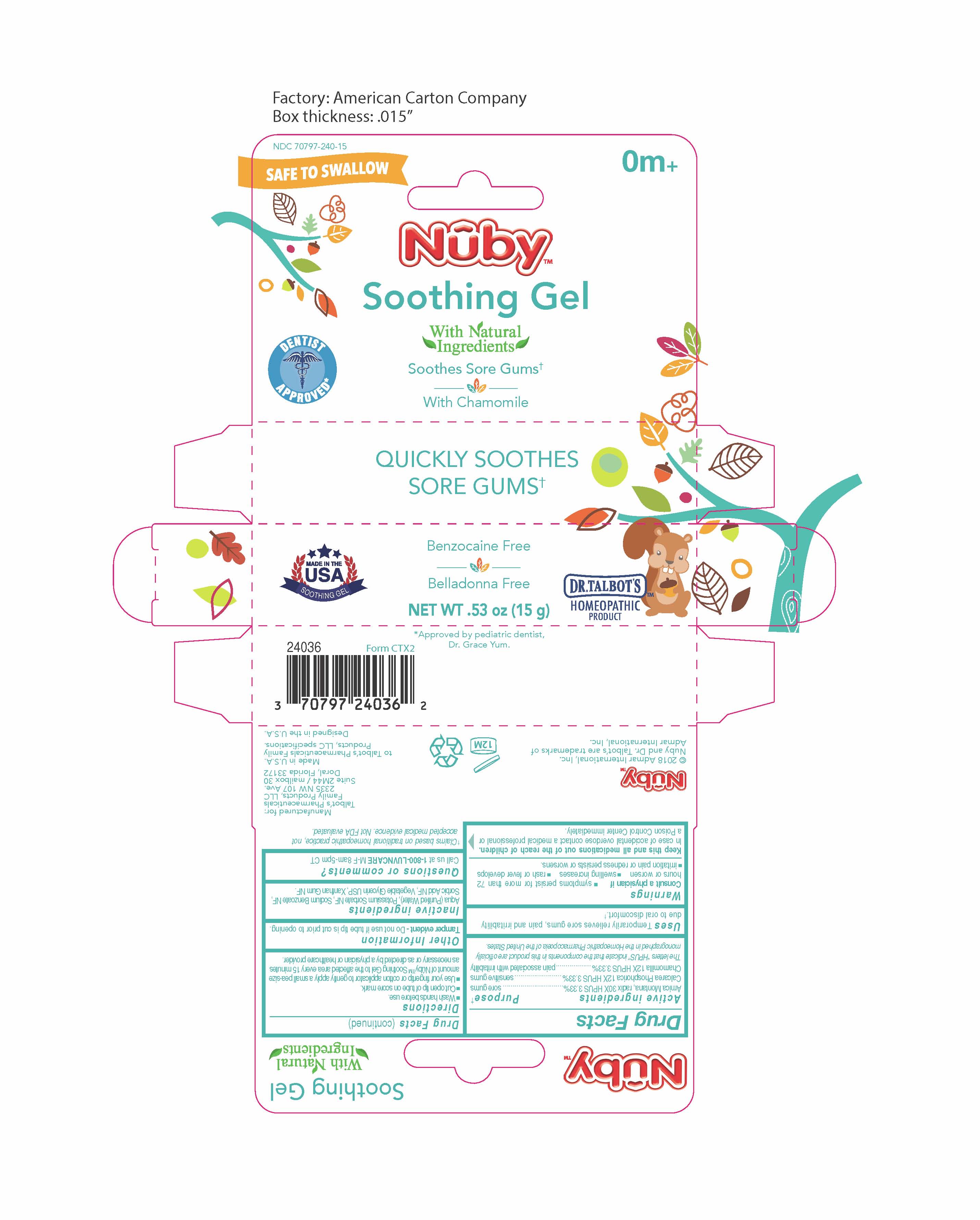 DRUG LABEL: Nuby Soothing Gel
NDC: 71240-240 | Form: GEL
Manufacturer: Ningbo Longwell Baby Products Co Ltd
Category: homeopathic | Type: HUMAN OTC DRUG LABEL
Date: 20231109

ACTIVE INGREDIENTS: MATRICARIA RECUTITA 12 [hp_X]/15 g; ARNICA MONTANA ROOT 30 [hp_X]/15 g; TRIBASIC CALCIUM PHOSPHATE 12 [hp_X]/15 g
INACTIVE INGREDIENTS: XANTHAN GUM; WATER; POTASSIUM SORBATE; GLYCERIN; SODIUM BENZOATE; SORBIC ACID

Active Ingredients

Arnica Montana, radix 30X HPUS 3.33%

Calcarea Phosphorica 12X HPUS 3.33%

Chamomilla 12X HPUS 3.33%

The letters “HPUS” indicate that the components in this product are officially monographed in the Homeopathic Pharmacopoeia of the United States.

Purpose

sore gums

sensitive gums

pain associated with irritability

Keep this and all medicines out of the reach of children.

Keep this and all medications out of the reach of children. In case of accidental overdose contact a medical professional or a Poison Control Center immediately.

Questions or comments?

Call us at 1-800-LUVNCARE M-F 8am-5pm CT

Other Information

Tamper evident - Do not use if tube tip is cut prior to opening.

Directions

• Wash hands before use.

• Cut open tip of tube on score mark.

• Use your fingertip or cotton applicator to gently apply a small pea-size amount of Nûby™ Soothing Gel to the affected area every 15 minutes as necessary or as directed by a physician or healthcare provider.

Inactive Ingredients

Aqua (Purified Water), Potassium Sorbate NF, Sodium Benzoate NF, Sorbic Acid NF, Vegetable Glycerin USP, Xanthan Gum NF.

Uses

Uses Temporarily relieves sore gums, pain and irritability due to oral discomfort.†

Warnings

Consult a physician if • symptoms persist for more than 72 hours or worsen • swelling increases • irritation pain or redness persists or worsens • rash or fever develops